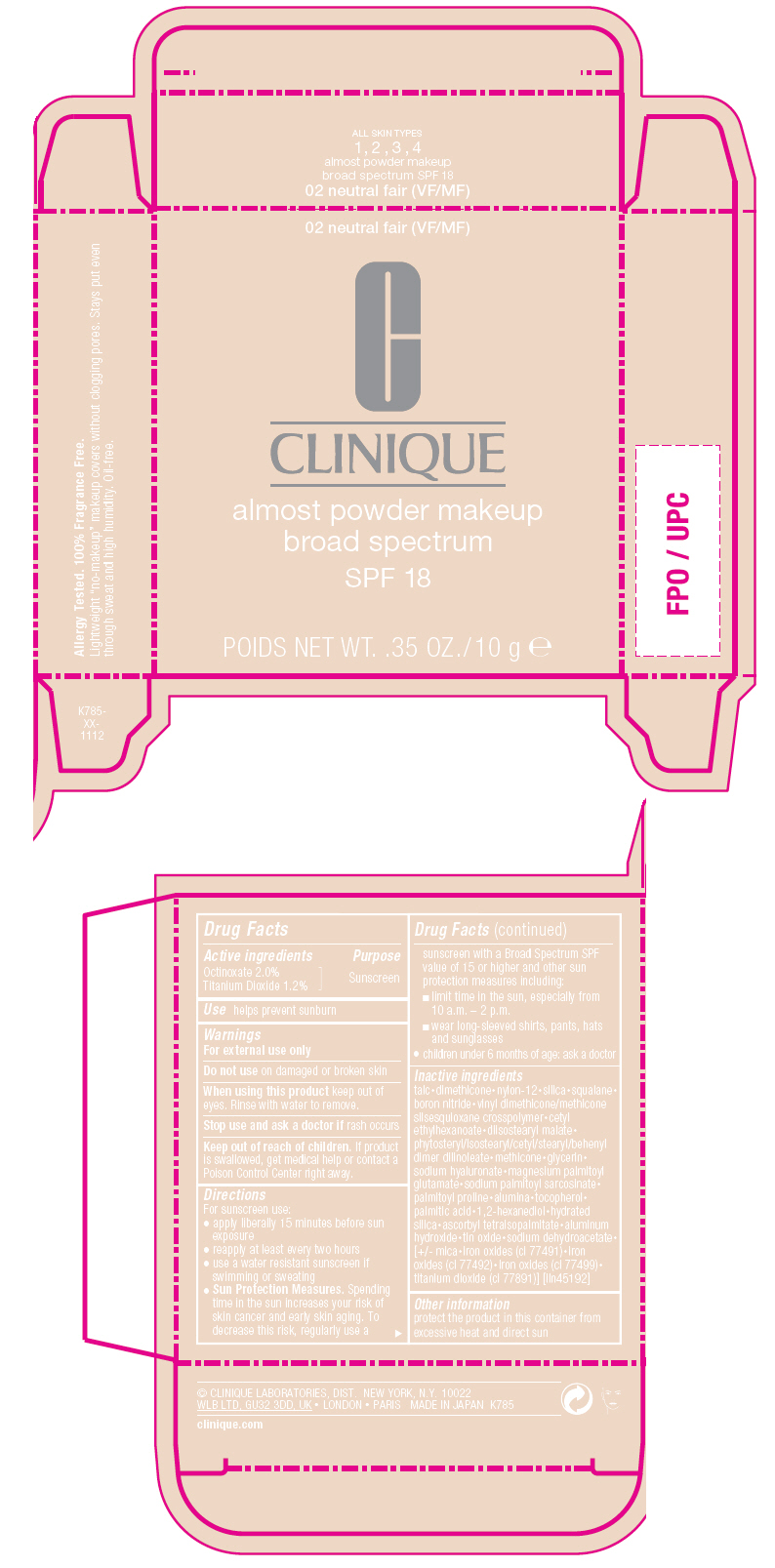 DRUG LABEL: ALMOST powder MAKEUP BROAD SPECTRUM SPF 18
NDC: 49527-060 | Form: POWDER
Manufacturer: CLINIQUE LABORATORIES LLC
Category: otc | Type: HUMAN OTC DRUG LABEL
Date: 20231011

ACTIVE INGREDIENTS: OCTINOXATE 2 g/100 g; TITANIUM DIOXIDE 1.2 g/100 g
INACTIVE INGREDIENTS: FERRIC OXIDE YELLOW; FERROSOFERRIC OXIDE; TALC; DIMETHICONE; NYLON-12; SILICON DIOXIDE; SQUALANE; BORON NITRIDE; VINYL DIMETHICONE/METHICONE SILSESQUIOXANE CROSSPOLYMER; FERRIC OXIDE RED; CETYL ETHYLHEXANOATE; DIISOSTEARYL MALATE; PHYTOSTERYL/ISOSTEARYL/CETYL/STEARYL/BEHENYL DIMER DILINOLEATE; METHICONE (20 CST); GLYCERIN; HYALURONATE SODIUM; MAGNESIUM PALMITOYL GLUTAMATE; SODIUM PALMITOYL SARCOSINATE; PALMITOYL PROLINE; ALUMINUM OXIDE; TOCOPHEROL; PALMITIC ACID; 1,2-HEXANEDIOL; HYDRATED SILICA; ASCORBYL TETRAISOPALMITATE; ALUMINUM HYDROXIDE; STANNIC OXIDE; SODIUM DEHYDROACETATE; MICA

ALMOST POWDER MAKEUP BROAD SPECTRUM SPF 18

Drug Facts

Active ingredients

Octinoxate 2.0%
Titanium Dioxide 1.2%

Purpose

Sunscreen

Use

helps prevent sunburn

Warnings

For external use only

Do not use on damaged or broken skin

When using this product keep out of eyes. Rinse with water to remove.

Stop use and ask a doctor if rash occurs

Keep out of reach of children. If product is swallowed, get medical help or contact a Poison Control Center right away.

Directions

For sunscreen use:

- apply liberally 15 minutes before sun exposure
- reapply at least every two hours
- use a water resistant sunscreen if swimming or sweating
- Sun Protection Measures. Spending time in the sun increases your risk of skin cancer and early skin aging. To decrease this risk, regularly use a sunscreen with a Broad Spectrum SPF value of 15 or higher and other sun protection measures including:
  - limit time in the sun, especially from 10 a.m. – 2 p.m.
  - wear long-sleeved shirts, pants, hats and sunglasses
- children under 6 months of age: ask a doctor

Inactive ingredients

talc•dimethicone•nylon-12•silica•squalane•boron nitride•vinyl dimethicone/methicone silsesquioxane crosspolymer•cetyl ethylhexanoate•diisostearyl malate•phytosteryl/isostearyl/cetyl/stearyl/behenyl dimer dilinoleate•methicone•glycerin•sodium hyaluronate•magnesium palmitoyl glutamate•sodium palmitoyl sarcosinate•palmitoyl proline•alumina•tocopherol•palmitic acid•1,2-hexanediol•hydrated silica•ascorbyl tetraisopalmitate•aluminum hydroxide•tin oxide•sodium dehydroacetate•[+/- mica•iron oxides (ci 77491)•iron oxides (ci 77492)•iron oxides (ci 77499)•titanium dioxide (ci 77891)] [iln45192]

Other information

protect the product in this container from excessive heat and direct sun

PRINCIPAL DISPLAY PANEL - 10 g Jar Carton

02 neutral fair (VF/MF)

CLINIQUE

almost powder makeup
broad spectrum
SPF 18

POIDS NET WT. .35 OZ./10 g e